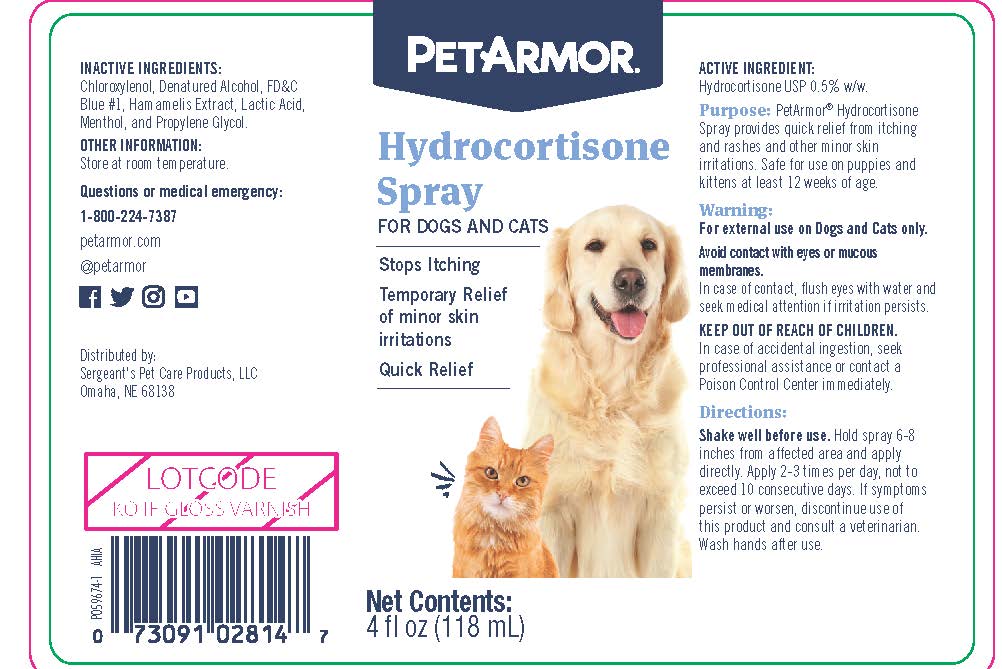 DRUG LABEL: Hydrocortisone
NDC: 21091-814 | Form: SPRAY
Manufacturer: Sergeant's Pet Care Products LLC
Category: animal | Type: OTC ANIMAL DRUG LABEL
Date: 20240419

ACTIVE INGREDIENTS: HYDROCORTISONE 0.59 g/118 mL

PetArmor Hydrocortisone

ACTIVE INGREDIENT:

Hydrocortisone USP 0.5% W/W.

Purpose:

PetArmor® Hydrocortisone Spray provides quick relief from itching and rashes and other minor skin irritations. Safe for use on puppies and kittens at least 12 weeks of age.

Warning:

For external use on Dogs and Cats only.

Avoid contact with eyes or mucous membranes.

In case of contact, flush eyes with water and seek medical attention if irritation persists.

In case of accidental ingestion seek professional assistance or contact a Poison Control Center immediately.

Directions:

Shake well before use. Hold spray 6-8 inches from affected area and apply directly. Apply 2-3 times per day, not to exceed 10 consecutive days. If symptoms persist or worsen, discontinue use of this product and consult a veterinarian. Wash hands after use.

INACTIVE INGREDIENTS:

Chloroxylenol, Denatured Alcohol, FD&C Blue #1, Hamamelis Extract, Lactic Acid, Menthol, and Propylene Glycol.

OTHER INFORMATION:

Store at room temperature.

Questions or medical emergency:

1-800-224-7387

petarmor.com

@petarmor